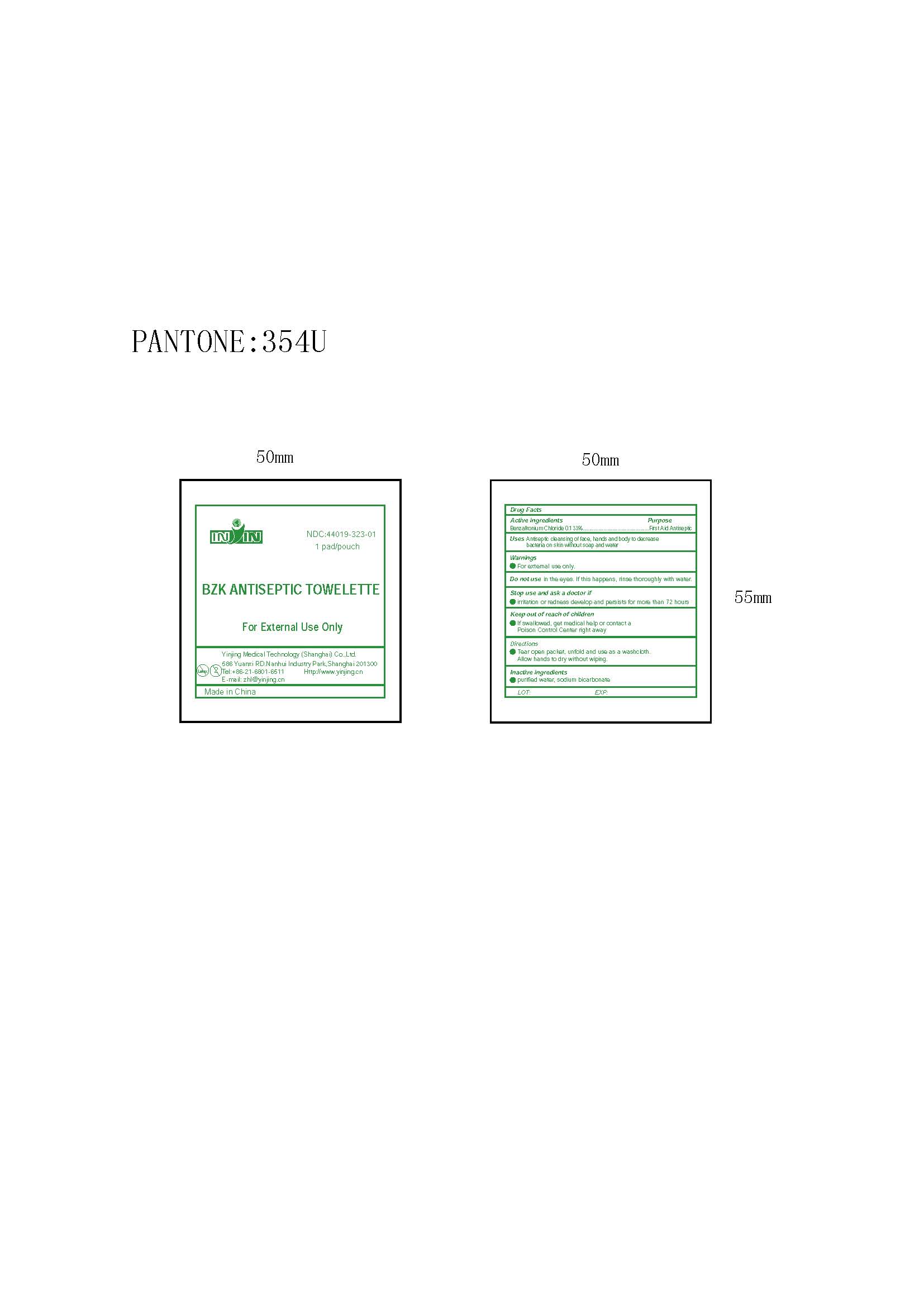 DRUG LABEL: BZK ANTISEPTIC TOWELETTE

NDC: 44019-323 | Form: SWAB
Manufacturer: Yinjing Medical Technology (Shanghai) Co., Ltd.
Category: otc | Type: HUMAN OTC DRUG LABEL
Date: 20171227

ACTIVE INGREDIENTS: BENZALKONIUM CHLORIDE 0.13 g/100 g
INACTIVE INGREDIENTS: WATER; SODIUM BICARBONATE

BZK ANTISEPTIC TOWELETTE

Active ingredient

Benzalkonium Chloride, 0.13% w/v

Purpose

First Aid Antiseptic

Use

First aid antiseptic to help prevent the risk of infection in minor cuts, scrapes and burns.

Warnings

For external use only.

Do not use

- in the eyes or apply over large areas of the body
- longer than 1 week unless directed by a doctor.

Consult a doctor

in case of deep or puncture wounds, animal bites, or serious burns.

Stop use and consult a doctor

if the condition persists or gets worse.

Keep out of reach of children.

If swallowed, get medical help or contact a Poison Control Center right away.

Directions

- Clean the affected area
- Apply a small amount of this product on the area 1 to 3 times daily
- May be covered with a sterile bandage when dry

Inactive ingredients

purified water, sodium bicarbonate

Shanghai Yinjing Medical Supplies Co., Ltd.
586 Yuanxi RD.Nanhui Industry Park,Shanghai 201300
Tel:+86-21-6801-6511 Http://www.yinjing.cn
E-mail: zhl@yinjing.cn
Made in China
LOT

PACKAGE LABEL

NDC：44019-323-01
inin 1 pad/pouch
BZK ANTISEPTIC TOWELETTE
For External Use Only